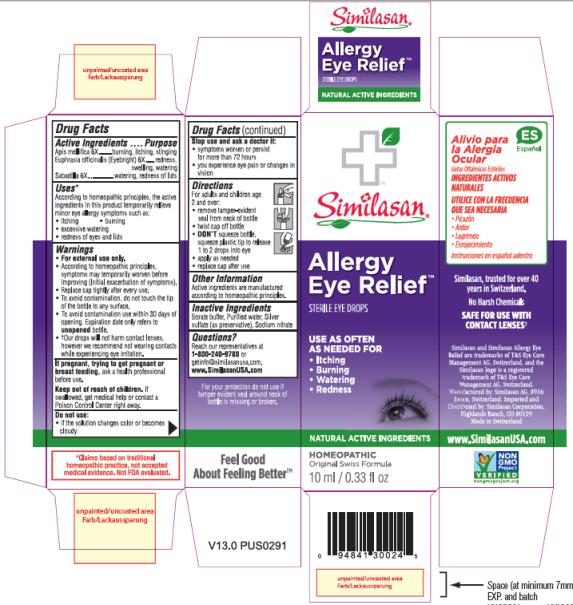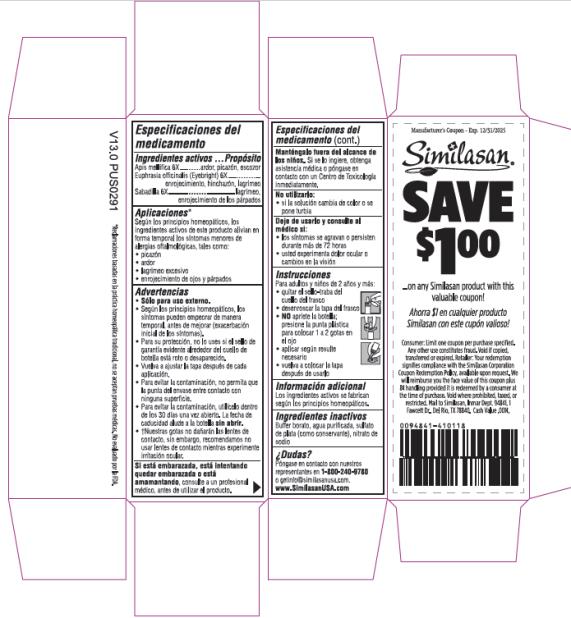 DRUG LABEL: Allergy Eye Relief
NDC: 53799-364 | Form: SOLUTION/ DROPS
Manufacturer: Similasan AG
Category: homeopathic | Type: HUMAN OTC DRUG LABEL
Date: 20230109

ACTIVE INGREDIENTS: APIS MELLIFERA 6 [hp_X]/0.45 mL; EUPHRASIA STRICTA 6 [hp_X]/0.45 mL; SCHOENOCAULON OFFICINALE SEED 6 [hp_X]/0.45 mL
INACTIVE INGREDIENTS: BORIC ACID; WATER; SODIUM NITRATE; SILVER SULFATE

Allergy Eye Relief

Drug Facts

Active Ingredient

Apis mellifica 6X

Purpose

burning, itching, stinging

Active Ingredient

Euphrasia officinalis (Eyebright) 6X

Purpose

redness, swelling, watering

Active Ingredient

Sabadilla 6X

Purpose

watering, redness of lids

Uses:

According to homeopathic principles, the active ingredients in this product temporarily relieve minor eye allergy symptoms such as:

- itching
- burning
- excessive watering
- redness of eyes and lids

Warnings:

- For external use only.
- According to homeopathic principles, symptoms may temporarily worsen before improving (Initial exacerbation of symptoms).
- Replace cap tightly after every use.
- To avoid contamination, do not touch the plastic tip to any surface.
- To avoid contamination use within 30 days of opening. Expiration date only refers to unopened bottle.
- †Our drops will not harm contact lenses, however we recommend not wearing contacts while experiencing eye irritation.

If pregnant, trying to get pregnant,or breast feeding,

ask a health professional before use.

Keep out of reach of children.

If swallowed, get medical help or contact a Poison Control Center right away.

Do not use:

- if the solution changes color or becomes cloudy

Stop use and ask a doctor if:

- symptoms worsen or persist for more than 72 hours
- you experience eye pain or changes in vision

Directions:

For adults and children age

2 and over:

- remove tamper-evident seal from neck of bottle
- twist cap off bottle
- DON’T squeeze bottle, squeeze plastic tip to release 1-2 drops into eye
- apply as needed
- replace cap after use

Other Information:

Active ingredients are manufactured according to homeopathic principles.

Inactive Ingredients:

Borate buffer, Purified water, Silver sulfate (as preservative), Sodium nitrate

Questions?

Reach our representatives at 1-800-240-9780 or getinfo@similasanusa.com.

www.SimilasanUSA.com

PRINCIPAL DISPLAY PANEL

Similasan

Allergy Eye Relief

STERILE EYE DROPS

10 ml / 0.33 fl oz